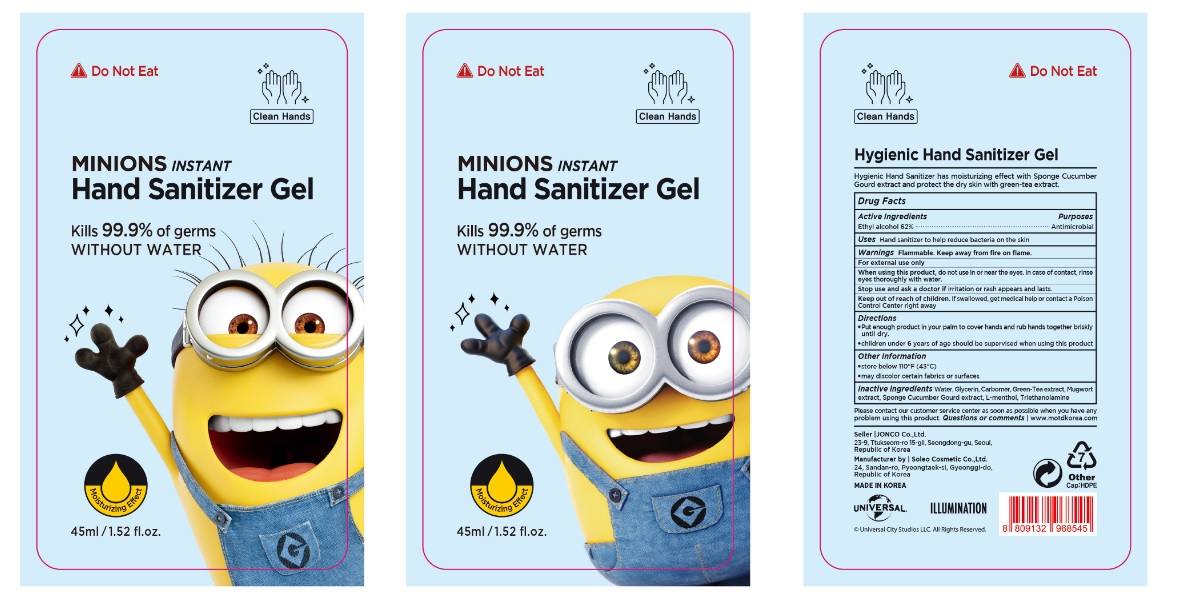 DRUG LABEL: MINIONS Instant Hand Sanitizer Gel
NDC: 73867-001 | Form: GEL
Manufacturer: JONCO Co., Ltd.
Category: otc | Type: HUMAN OTC DRUG LABEL
Date: 20200323

ACTIVE INGREDIENTS: ALCOHOL 0.62 mg/1 mL
INACTIVE INGREDIENTS: WATER; GLYCERIN; CARBOMER HOMOPOLYMER, UNSPECIFIED TYPE; GREEN TEA LEAF; ARTEMISIA PRINCEPS LEAF; LEVOMENTHOL; TROLAMINE

MINIONS Instant Hand Sanitizer Gel

Active ingredient

Ethyl alcohol 62%

Purpose

Antimicrobial

Use

- Hand sanitizer to help reduce bacteria on the skin

Warnings

Flammable. Keep away from fire or flame.

For external use only

When using this product do not use in or near the eyes. In case of contact, rinse eyes thoroughly with water.

Stop use and ask a doctor if irritation or rash appears and lasts

Keep out of reach of children. If swallowed, get medical help or contact a Poison Control Center right away.

Directions

- Put nough produt in your palm to cover hands and rub hands together briskly until dry.
- Children under 6 years of age should be supervised when using PURELL

Other information

- Store below 110°F (43°C)
- May discolor certain fabrics or surfaces

Inactive ingredients

Water, Glycerin, Carbomer, Green Tea Extract, Mugwort extract, Sponge Cucumber Gourd extract, L-menthol, Triethanolamine